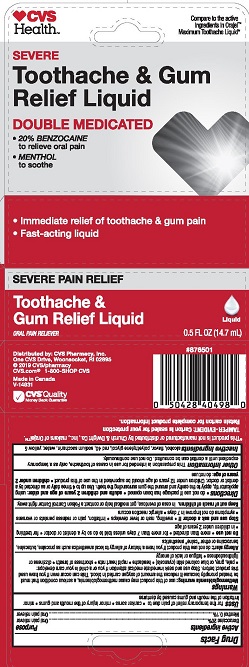 DRUG LABEL: Toothache and Gum Relief
NDC: 69842-353 | Form: LIQUID
Manufacturer: CVS Pharmacy
Category: otc | Type: HUMAN OTC DRUG LABEL
Date: 20250120

ACTIVE INGREDIENTS: BENZOCAINE 20 g/100 mL; MENTHOL 0.1 g/100 mL
INACTIVE INGREDIENTS: POLYETHYLENE GLYCOL, UNSPECIFIED; FD&C YELLOW NO. 5; WATER; FD&C RED NO. 40; ALCOHOL; SACCHARIN SODIUM

5820375 CVS Toothache & Gum Relief Liquid

Drug Facts

Active ingredients

Benzocaine 20%

Menthol 0.1%

Purpose

Oral pain reliever

Oral pain reliever

Uses

for the temporary relief of pain due to

- canker sores
- minor injury of the mouth and gums
- minor irritation of the mouth and gums caused by dentures

Warnings

Methemoglobinemia warning: use of this product may cause methemoglobinemia, a serious condition that must be treated promptly because it reduces the amount of oxygen carried in blood. This can occur even if you have used this product before. Stop use and seek immediate medical attention if you or a child in your care develops:

- pale, gray or blue colored skin (cyanosis)
- headache
- rapid heart rate
- shortness of breath
- dizziness or lightheadedness
- fatigue or lack of energy

Allergy alert: do not use this product if you have a history of allergy to local anesthetics such as procaine, butacaine, benzocaine or other "caine" anesthetics

Do not use

- more than directed
- for more than 7 days unless told to do so by a dentist or doctor
- for teething
- in children under 2 years of age

Stop use and ask a doctor if

- swelling, rash or fever develops
- irritation, pain or redness persists or worsens
- symptoms do not improve in 7 days
- allergic reaction occurs

Keep out of reach of children. In case of overdose, get medical help or contact a Poison Control Center right away.

Directions

- do not use if package has been opened
- adults and children 2 years of age and older: using applicator tip, apply to the cavity and around the gum surrounding the teeth. Use up to 4 times daily or as directed by a dentist or doctor. Children 12 years of age should be supervised in the use of this product
- children under 2 years of age: do not use

Other information This preparation is intended for use in cases of toothache, only as a temporary expedient until a dentist can be consulted. Do not use continuously.

INACTIVE INGREDIENT

Inactive ingredients alcohol, flavor, polyethylene glycol, red 40, sodium saccharin, water, yellow 5

TAMPER-EVIDENT: Carton is sealed for your protection.

Retain carton for complete product information.

Distributed by: CVS Pharmacy, Inc.

One CVS Drive, Woonsocket, RI 02895

CVS.com 1-800-SHOP-CVS

Made in Canada

PACKAGE LABEL

CVS Health™

SEVERE PAIN RELIEF

Toothache & Gum Relief Liquid

ORAL PAIN RELIEVER

DOUBLE MEDICATED

- 20% BENZOCAINE to relieve oral pain
- MENTHOL to soothe

0.5 FL OZ (14.7 mL)